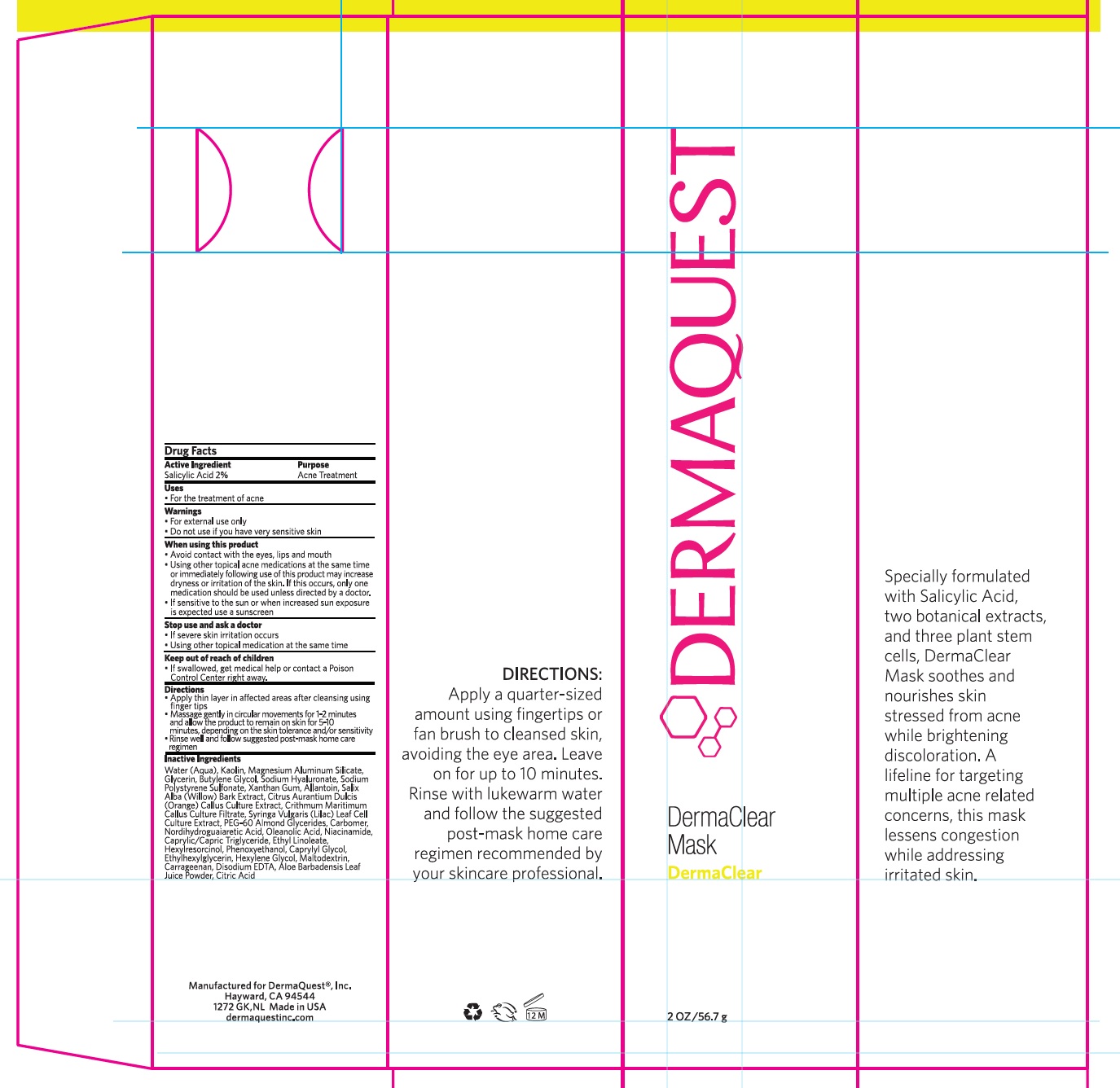 DRUG LABEL: Dermaclear Mask
NDC: 62742-4074 | Form: CREAM
Manufacturer: Allure Labs Inc,
Category: otc | Type: HUMAN OTC DRUG LABEL
Date: 20241204

ACTIVE INGREDIENTS: SALICYLIC ACID 20 mg/1 g
INACTIVE INGREDIENTS: SYRINGA VULGARIS WHOLE; MASOPROCOL; OLEANOLIC ACID; CITRIC ACID MONOHYDRATE; SALIX ALBA BARK; PHENOXYETHANOL; SODIUM POLYSTYRENE SULFONATE; MEDIUM-CHAIN TRIGLYCERIDES; CARRAGEENAN; WATER; KAOLIN; GLYCERIN; MAGNESIUM ALUMINUM SILICATE; XANTHAN GUM; ALLANTOIN; ORANGE; BUTYLENE GLYCOL; HYALURONATE SODIUM; CRITHMUM MARITIMUM; PEG-60 ALMOND GLYCERIDES; CARBOMER HOMOPOLYMER, UNSPECIFIED TYPE; CAPRYLYL GLYCOL; HEXYLENE GLYCOL; MALTODEXTRIN; ALOE VERA LEAF; NIACINAMIDE; ETHYL LINOLEATE; HEXYLRESORCINOL; ETHYLHEXYLGLYCERIN; EDETATE DISODIUM ANHYDROUS

Drug Facts

Active Ingredient:

Salicylic Acid- 2%

Purpose: Acne Treatment

Uses:

For the treatment of acne.

Warnings:

For external use only.

Do not use if you have very sensitive skin.

When using this product:

- Avoid contact with the eyes, lips and mouth.
- Using other topical acne medications at the same time or immediately following use of this product may increase dryness or irritation of the skin. If this occurs, only one medication should be used unless directed by a doctor.
- If sensitive to the sun or when increased sun exposure is expected use a sunscreen.

Stop use and ask a doctor:

- If severe skin irritation occurs.
- Using other topical medication at the same time.

Keep out of reach of children:

If swallowed, get medical help or contact a Poison control center right away.

Stop use and ask a Doctor

- If severe skin irritation occurs.
- Using other topical medication at the same time.

Directions:

- Apply thin layer in affected areas after cleansing using finger tips.
- Massage gently in circular movements for 1-2 minutes and allow the product to remain on skin for 5-10 minutes, depending on the skin tolerance and/or sensitivity.
- Rinse well and follow suggested post-mask home care regimen.

INACTIVE INGREDIENT

Inavtive Ingredients:

Water (Aqua), Kaolin, Magnesium Aluminum Silicate, Glycerin, Butylene Glycol, Sodium Hyaluronate, Sodium Polystyrene Sulfonate, Xanthan Gum, Allantoin, Salix Alba (Willow) Bark Extract, Citrus Aurantium Dulcis (Orange) Callus Culture Extract , Crithmum Maritimum Callus Culture Filtrate, Syringa Vulgaris (Lilac) Leaf Cell Culture Extract, PEG-60 Almond Glycerides, Carbomer, Nordihydroguaiaretic Acid, Oleanolic Acid, Niacinamide, Caprylic/Capric Triglyceride, Ethyl Linoleate, Hexylresorcinol, Phenoxyethanol, Caprylyl Glycol, Ethylhexylglycerin, Hexylene Glycol, Maltodextrin, Carrageenan , Disodium EDTA, Aloe Barbadensis Leaf Juice Powder, Citric Acid,

PACKAGE LABEL

Manufactured for DermaQuest®, Inc.

Hayward, CA 94544

1272 GK,NL Made in USA

dermaquestinc.com